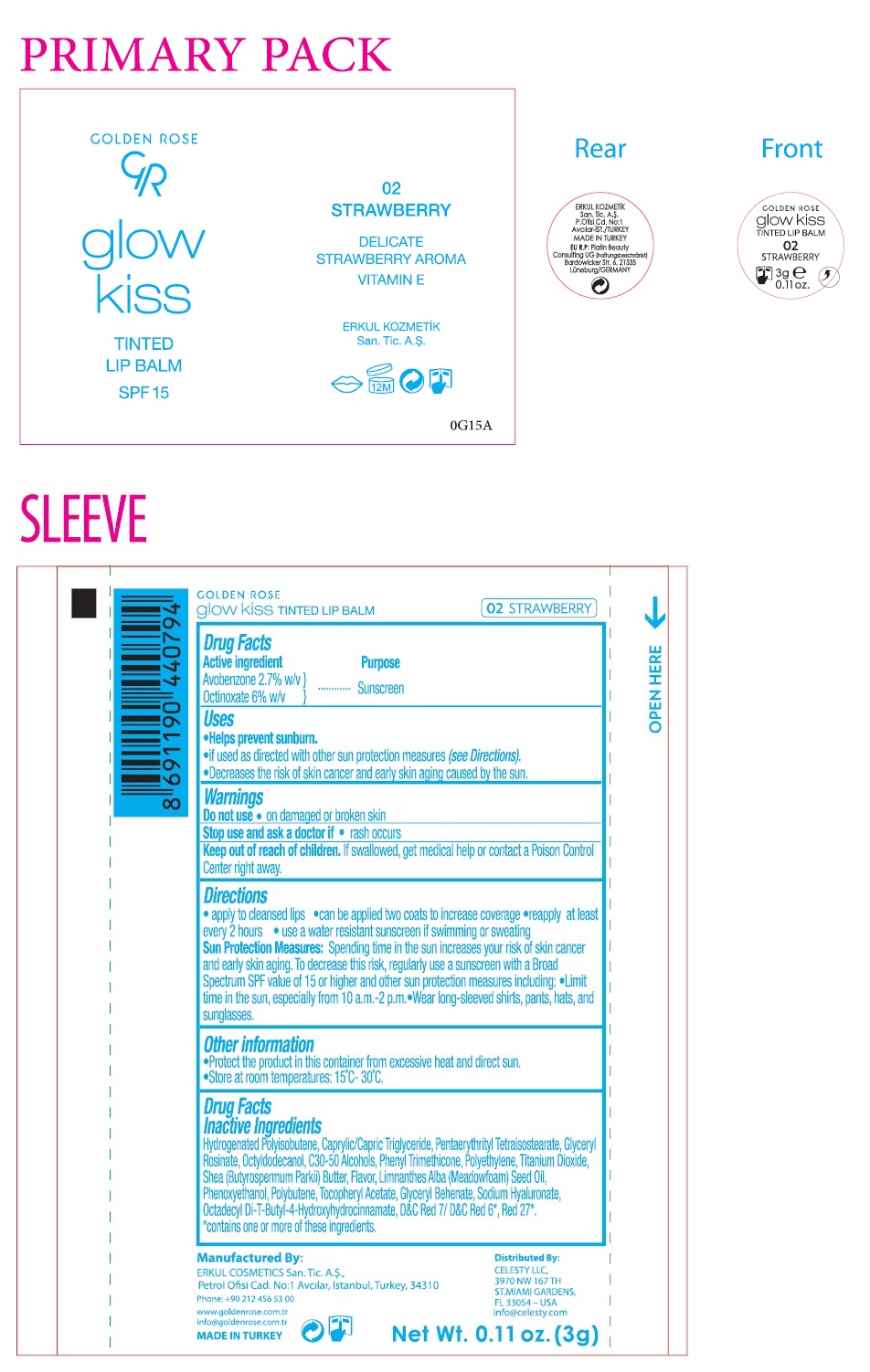 DRUG LABEL: GOLDEN ROSE GLOW KISS TINTED LIP BALM STRAWBERRY
NDC: 82715-110 | Form: LIPSTICK
Manufacturer: ERKUL KOZMETIK SANAYI VE TICARET ANONIM SIRKETI
Category: otc | Type: HUMAN OTC DRUG LABEL
Date: 20250808

ACTIVE INGREDIENTS: AVOBENZONE 2.7 g/100 g; OCTINOXATE 6 g/100 g
INACTIVE INGREDIENTS: HYDROGENATED POLYISOBUTENE (1300 MW); MEDIUM-CHAIN TRIGLYCERIDES; PENTAERYTHRITYL TETRAISOSTEARATE; GLYCERYL ROSINATE; OCTYLDODECANOL; C30-50 ALCOHOLS; PHENYL TRIMETHICONE; HIGH DENSITY POLYETHYLENE; TITANIUM DIOXIDE; SHEA BUTTER; MEADOWFOAM SEED OIL; PHENOXYETHANOL; POLYBUTENE (1400 MW); .ALPHA.-TOCOPHEROL ACETATE; GLYCERYL MONOBEHENATE; HYALURONATE SODIUM; OCTADECYL DI-TERT-BUTYL-4-HYDROXYHYDROCINNAMATE; D&C RED NO. 7; D&C RED NO. 6; D&C RED NO. 27

GOLDEN ROSE glow kiss TINTED LIP BALM STRAWBERRY

Active ingredient

Avobenzone 2.7% w/v
Octinoxate 6% w/v

Purpose

Sunscreen

Uses

• Helps prevent sunburn.
• if used as directed with other sun protection measures (see Directions).
• Decreases the risk of skin cancer and early skin aging caused by the sun.

Warnings

Do not use • on damaged or broken skin

Stop use and ask a doctor if • rash occurs

Keep out of reach of children. If swallowed, get medical help or contact a Poison Control Center right away.

Directions

• apply to cleansed lips • can be applied two coats to increase coverage • reapply at least every 2 hours • use a water resistant sunscreen if swimming or sweating
Sun Protection Measures: Spending time in the sun increases your risk of skin cancer and early skin aging. To decrease this risk, regularly use a sunscreen with a Broad Spectrum SPF value of 15 or higher and other sun protection measures including: • Limit time in the sun, especially from 10 a.m. - 2 p.m. • Wear long-sleeved shirts, pants, hats, and sunglasses.

Other information

• Protect the product in this container from excessive heat and direct sun.
• Store at room temperatures: 15°C- 30°C.

Drug Facts Inactive Ingredients

Hydrogenated Polyisobutene, Caprylic/Capric Triglyceride, Pentaerythrityl Tetraisostearate, Glyceryl Rosinate, Octyldodecanol, C30-50 Alcohols, Phenyl Trimethicone, Polyethylene, Titanium Dioxide, Shea (Butyrospermum Parkii) Butter, Flavor, Limnanthes Alba (Meadowfoam) Seed Oil, Phenoxyethanol, Polybutene, Tocopheryl Acetate, Glyceryl Behenate, Sodium Hyaluronate, Octadecyl Di-T-Butyl -4-Hydroxyhydrocinnamate, D&C Red 7/ D&C Red 6*, Red 27*.
*contains one or more of these ingredients.

SPF 15

DELICATE
STRAWBERRY AROMA
VITAMIN E

Manufactured By:
ERKUL COSMETICS San. Tic. A.S.,
Petrol Ofisi Cad. No:1 Avcılar, Istanbul, Turkey, 34310

Phone: +90 212 456 53 00

www.goldenrose.com.tr
info@goldenrose.com.tr

MADE IN TURKEY

Distributed By:
CELESTY LLC,
3970 NW 167 TH
ST.MIAMI GARDENS,
FL 33054 – USA
info@celesty.com

EU R.P: Platin Beauty
Consulting UG (haftungsbeschränkt)
Bardowicker Str. 6, 21335
Lüneburg/GERMANY